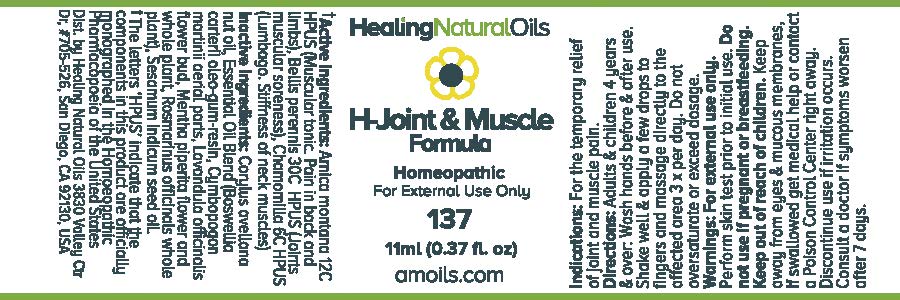 DRUG LABEL: H-Joint and Muscle Formula
NDC: 61077-137 | Form: OIL
Manufacturer: Healing Natural Oils LLC
Category: homeopathic | Type: HUMAN OTC DRUG LABEL
Date: 20171227

ACTIVE INGREDIENTS: ARNICA MONTANA 12 [hp_C]/11 mL; BELLIS PERENNIS 30 [hp_C]/11 mL; MATRICARIA RECUTITA 6 [hp_C]/11 mL
INACTIVE INGREDIENTS: EUROPEAN HAZELNUT OIL; FRANKINCENSE OIL; PALMAROSA OIL; LAVANDULA ANGUSTIFOLIA FLOWERING TOP; PEPPERMINT; ROSMARINUS OFFICINALIS WHOLE; SESAME OIL

Active Ingredients:

Arnica Montana 12C HPUS, Bellis perennis 30C HPUS, Chamomilla 6C HPUS

Purpose

Arnica Montana 12C HPUS (Muscular tonic. Pain in back and limbs), Bellis perennis 30C HPUS (Joints muscular soreness), Chamomilla 6C HPUS (Lumbago. Stiffness of neck muscles)

The letters ‘HPUS’ indicate that the components in this product are officially monographed in the Homoeopathic Pharmacopoeia of the United States

Inactive Ingredients:

Corylus avellana nut oil, Essential Oil Blend (Boswellia carterii oleo-gum-resin, Cymbopogon martinii aerial parts, Lavandula officinalis flower bud, Mentha piperita flower and whole plant, Rosmarinus officinals whole plant), Sesamum indicum seed oil.

Indications:

For the temporary relief of joint and muscle pain.

Directions:

Adults and Children 4 years and over: Wash hands before and after use. Shake well and apply a few drops to fingers and massage directly to the affected area 3x per day. Do not oversaturate or exceed dosage.

Warnings:

For external use only.
Perform skin test prior to initial use.

Do not use if pregnant or breastfeeding.

Keep out of reach of children.

OTHER SAFETY INFORMATION

Keep away from eyes and mucous membranes. If swallowed get medical help or contact a Poison Control Center right away.

Discontinue use if irritation occurs.

ASK DOCTOR

Consult a doctor if symptoms worsen after 7 days.

DESCRIPTION

Dist. by Healing Natural Oils 3830 Valley Ctr Dr, #705-526, San Diego, CA 92130, USA

PACKAGE LABEL

Healing Natural Oils

H-Joint & Muscle
Formula

Homeopathic

For External Use Only

137

11ml (0.37 fl. oz)

amolis.com